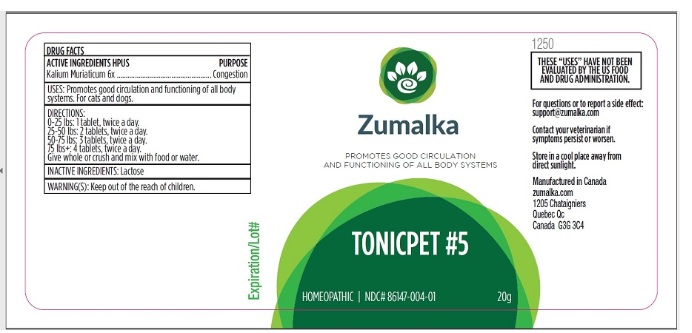 DRUG LABEL: TONICPET 5
NDC: 86147-004 | Form: PELLET
Manufacturer: Groupe Cyrenne Inc.
Category: homeopathic | Type: OTC ANIMAL DRUG LABEL
Date: 20251120

ACTIVE INGREDIENTS: POTASSIUM CHLORIDE 6 [hp_X]/20 g
INACTIVE INGREDIENTS: LACTOSE, UNSPECIFIED FORM

Active ingredient Purpose

Kalium Muriaticum 6x Congestion

Uses

Promotes good circulation and functioning of all body systems. For cats and dogs only.

Warnings

Store at room temperature. Keep out of reach of children.

Direction

0-25 lbs: 1 pellet, twice a day.
25-50 lbs: 2 pellets, twice a day.
50-75 lbs: 3 pellets, twice a day.
75 lbs+: 4 pellets, twice a day.

Give whole or crush and mix with food or water.

Inactive ingredient

Lactose

Other information

The letters "HPUS" indicate that the active ingredients are in the official Homeopathic Pharmacopoeia of the United States. Homeopathic remedy. Store at room temperature.